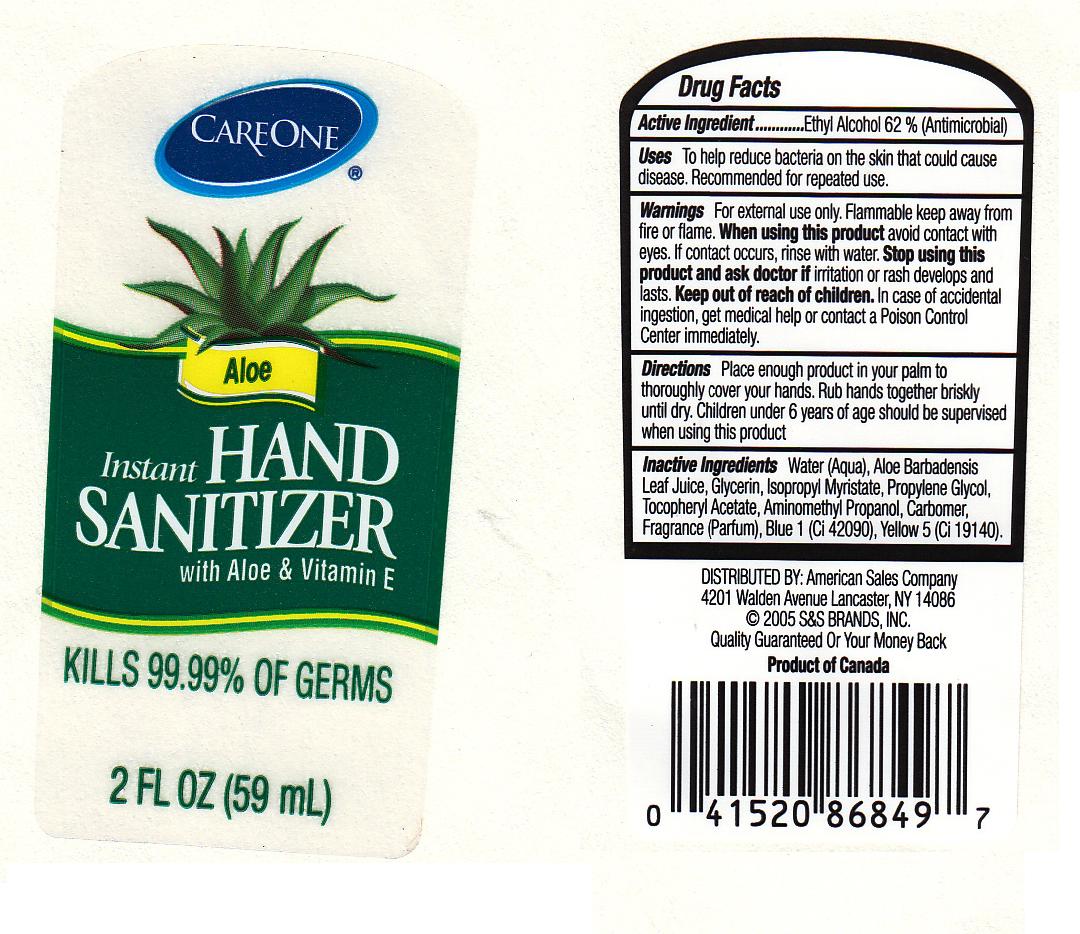 DRUG LABEL: CAREONE INSTANT HAND SANITIZER WITH ALOE AND VITAMIN E
NDC: 41520-223 | Form: GEL
Manufacturer: AMERICAN SALES COMPANY
Category: otc | Type: HUMAN OTC DRUG LABEL
Date: 20110708

ACTIVE INGREDIENTS: ALCOHOL 62 mL/100 mL
INACTIVE INGREDIENTS: WATER; GLYCERIN; ISOPROPYL MYRISTATE; PROPYLENE GLYCOL; .ALPHA.-TOCOPHEROL ACETATE, D-; AMINOMETHYLPROPANOL; CARBOMER 934; ALOE VERA LEAF; FD&C BLUE NO. 1; FD&C YELLOW NO. 5

DRUG FACTS

ACTIVE INGREDIENT

ETHYL ALCOHOL 62 PERCENT

PURPOSE

ANTIMICROBIAL

USES

TO HELP REDUCE BACTERIA ON THE SKIN THAT COULD CAUSE DISEASE. RECOMMENDED FOR REPEATED USE.

WARNINGS

FOR EXTERNAL USE ONLY. FLAMMABLE, KEEP AWAY FROM FIRE OR FLAME.

WHEN USING THIS PRODUCT AVOID CONTACT WITH EYES.IF CONTACT OCCURS, RINSE WITH WATER.

STOP USE

STOP USING THIS PRODUCT AND ASK DOCTOR IF IRRITATION OR RASH DEVELOPS AND LASTS.

KEEP OUT OF REACH OF CHILDREN. IN CASE OF ACCIDENTAL INGESTION, GET MEDICAL HELP OR CONTACT A POISON CONTROL CENTER IMMEDIATELY.

DIRECTIONS

PLACE ENOUGH PRODUCT IN YOUR PALM TO COVER YOUR HANDS. RUB HANDS TOGETHER BRISKLY UNTIL DRY. CHILDREN UNDER 6 YEARS OF AGE SHOULD BE SUPERVISED WHEN USING THIS PRODUCT.

INACTIVE INGREDIENTS

WATER, ALOE BARBADENSIS LEAF JUICE, GLYCERIN, ISOPROPYL MYRISTATE, PROPYLENE GLYCOL, TOCOPHERYL ACETATE, AMINOMETHYL PROPANOL, CARBOMER,

FRAGRANCE, BLUE 1 (CI 42090), YELLOW 5 (CI 19140).